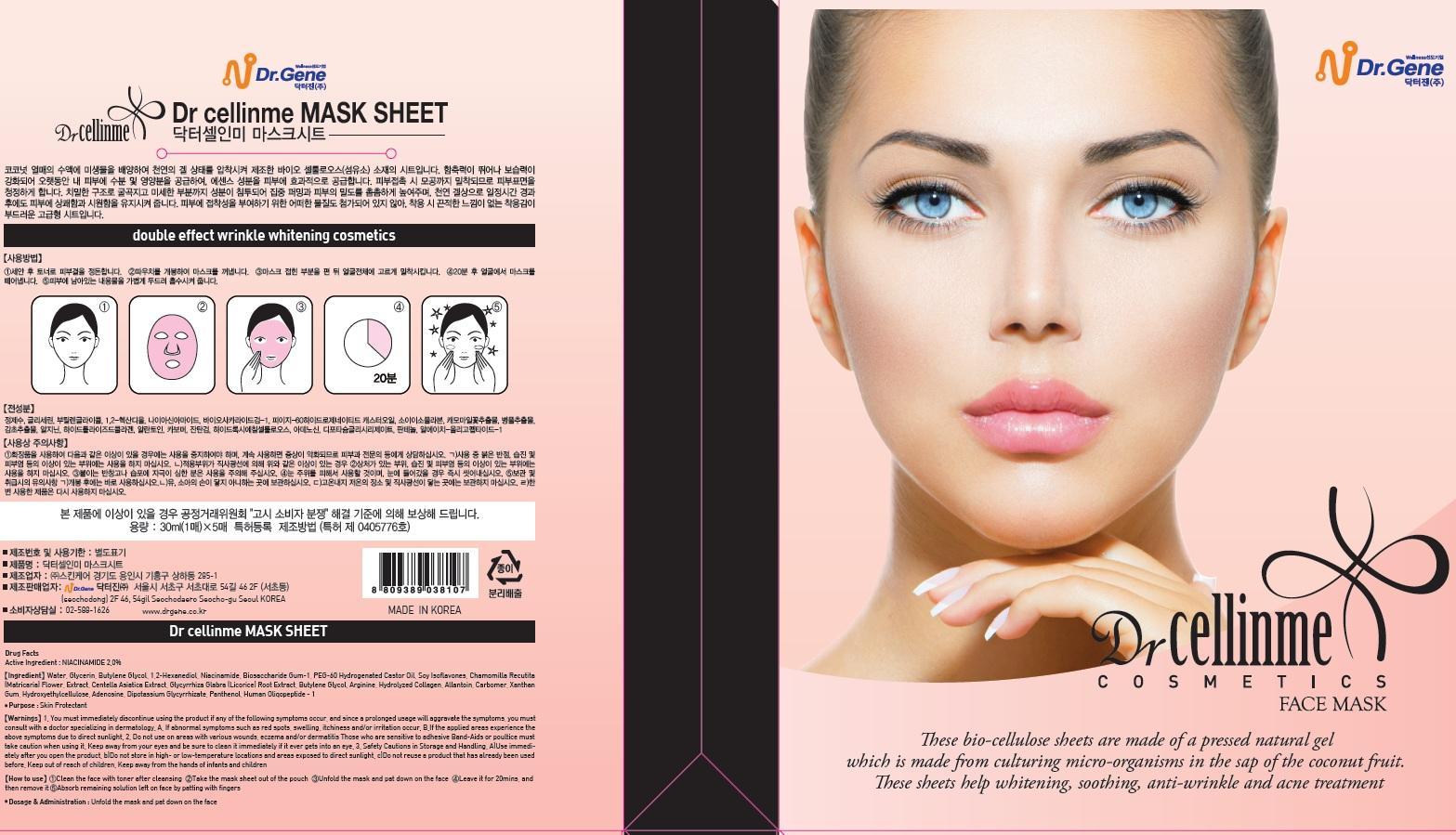 DRUG LABEL: Dr Cellinme Mask Sheet
NDC: 69783-020 | Form: PATCH
Manufacturer: Dr.Gene Co.,Ltd
Category: otc | Type: HUMAN OTC DRUG LABEL
Date: 20150728

ACTIVE INGREDIENTS: Niacinamide 0.6 mg/5 1
INACTIVE INGREDIENTS: Water; Glycerin

ACTIVE INGREDIENT

Active Ingredient: Niacinamide 2.0%

INACTIVE INGREDIENT

Inactive Ingredients: Water, Glycerin, Butylene Glycol, 1,2-Hexanediol, Biosaccharide Gum-1, PEG-60 Hydrogenated Castor Oil, Soy Isoflavones, Chamomilla Recutita (Matricaria) Flower Extract, Centella Asiatica Extract, Glycyrrhiza Glabra (Licorice) Root Extract, Butylene Glycol, Arginine, Hydrolyzed Collagen, Allantoin, Carbomer, Xanthan Gum, Hydroxyethylcellulose, Adenosine, Dipotassium Glycyrrhizate, Panthenol, Human Oliqopeptide - 1

PURPOSE

Purpose: Skin Protectant

WARNINGS

Warnings: 1. You must immediately discontinue using the product if any of the following symptoms occur, and since a prolonged usage will aggressive the symptoms, you must consult with a doctor specializing in dermatology. A. If abnormal symptoms such as red spots, swelling, itchiness and/or irritation occur. B. If the applied experience the above symptoms due to direct sunlight. 2. Do not use on areas with various wounds, eczema and/or dermatitis those who are sensitive to adhesive band-aids or poultice must take caution when using it. Keep away from your eyes and be sure to clean it immediately if it ever gets into an eye. 3. Safety cautions in storage and handling. A. Use immediately after you open the product. B. Do not store in high or low temperature locations and areas exposed to direct sunlight. C. Do not reuse a product that has already been used before. Keep out of reach of children. Keep away from the hands of infants and children.

Keep out of reach of children. Keep away from the hands of infants and children.

How to use: 1. Clean the face with toner after cleansing 2. Take the mask sheet out of the pouch 3. Unfold the mask and pat down on the face 4. Leave it for 20mins, and then remove it 5. Absorb remaining solution left on face by patting with fingers

DOSAGE & ADMINISTRATION

Dosage & Administration: Unfold the mask and pat down on the face